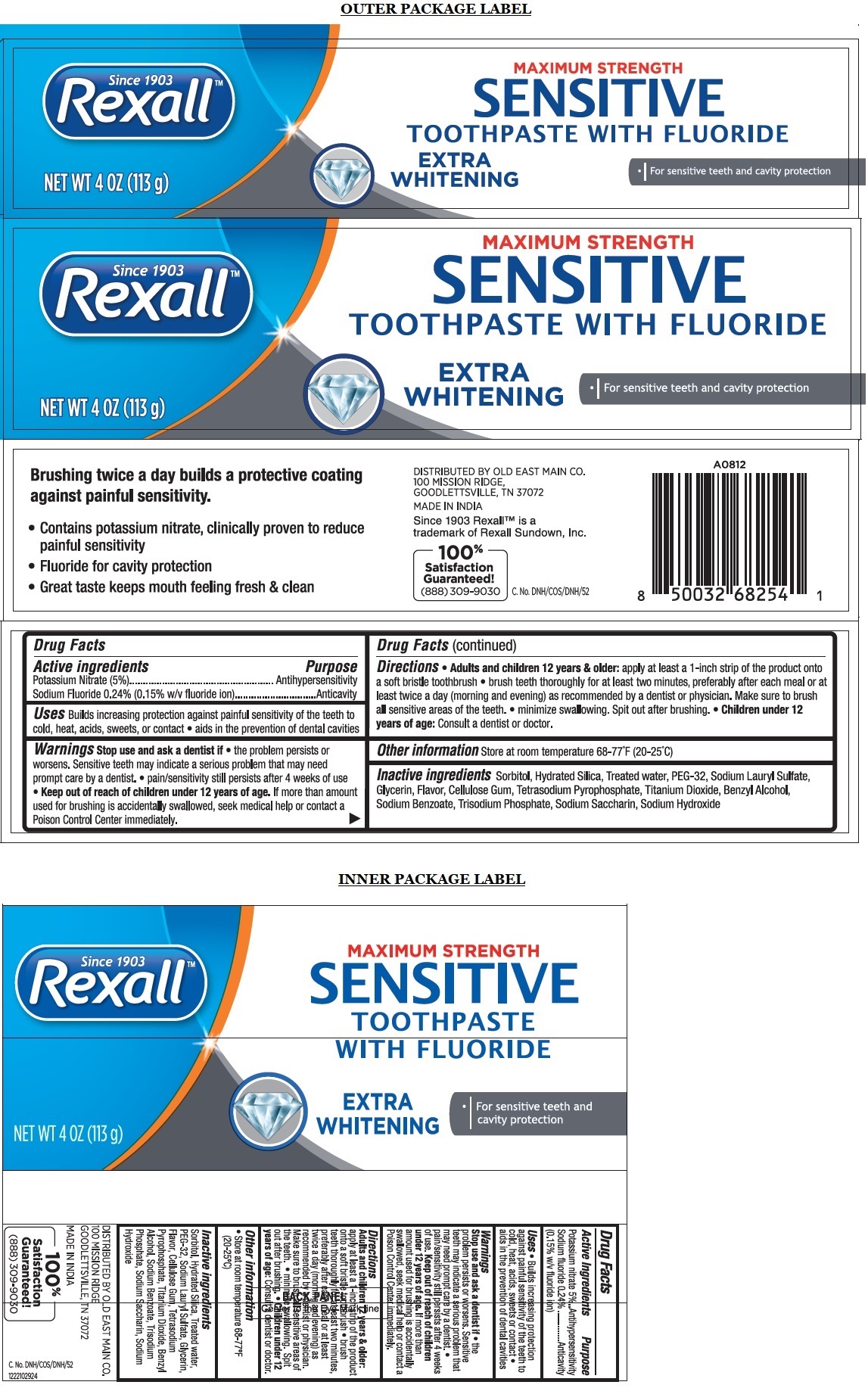 DRUG LABEL: Rexall Sensitive Extra Whitening
NDC: 55910-817 | Form: PASTE, DENTIFRICE
Manufacturer: Old East Main CO.
Category: otc | Type: HUMAN OTC DRUG LABEL
Date: 20241014

ACTIVE INGREDIENTS: POTASSIUM NITRATE 5 g/100 g; SODIUM FLUORIDE 0.24 g/100 g
INACTIVE INGREDIENTS: SORBITOL; HYDRATED SILICA; WATER; POLYETHYLENE GLYCOL 1600; SODIUM LAURYL SULFATE; GLYCERIN; CARBOXYMETHYLCELLULOSE SODIUM, UNSPECIFIED; SODIUM PYROPHOSPHATE; TITANIUM DIOXIDE; BENZYL ALCOHOL; SODIUM BENZOATE; SODIUM PHOSPHATE, TRIBASIC, ANHYDROUS; SACCHARIN SODIUM; SODIUM HYDROXIDE

Rexall™ SENSITIVE TOOTHPASTE WITH FLUORIDE - EXTRA WHITENING

Active ingredients

Potassium Nitrate (5%)
Sodium Fluoride 0.24% (0.15% w/v fluoride ion)

Purpose

Antihypersensitivity
Anticavity

Uses

Builds increasing protection against painful sensitivity of the teeth to cold, heat, acids, sweets, or contact • aids in the prevention of dental cavities

Warnings

Stop use and ask a dentist if • the problem persists or worsens. Sensitive teeth may indicate a serious problem that may need prompt care by a dentist • pain/sensitivity still persists after 4 weeks of use

• Keep out of reach of children under 12 years of age. If more than amount used for brushing is accidentally swallowed, seek medical help or contact a Poison Control Center immediately.

Directions

• Adults and children 12 years & older: apply at least a 1-inch strip of the product onto a soft bristle toothbrush • brush teeth thoroughly for at least two minutes, preferably after each meal or at least twice a day (morning and evening) as recommended by a dentist or physician. Make sure to brush all sensitive areas of the teeth. • minimize swallowing. Spit out after brushing. • Children under 12 years of age: Consult a dentist or doctor.

Other information

Store at room temperature 68-77°F (20-25°C)

Inactive ingredients

Sorbitol, Hydrated Silica, Treated water, PEG-32, Sodium Lauryl Sulfate, Glycerin, Flavor, Cellulose Gum, Tetrasodium Pyrophosphate, Titanium Dioxide, Benzyl Alcohol, Sodium Benzoate, Trisodium Phosphate, Sodium Saccharin, Sodium Hydroxide

MAXIMUM STRENGTH

TOOTHPASTE WITH FLUORIDE

• For sensitive teeth and cavity protection

Brushing twice a day builds a protective coating against painful sensitivity.

• Contains potassium nitrate, clinically proven to reduce painful sensitivity
• Fluoride for cavity protection
• Great taste keeps mouth feeling fresh & clear

Since 1903 Rexall™ is a trademark of Rexall Sundown, Inc.

100% satisfaction Guaranteed!
(888) 309-9030

DISTRIBUTED BY OLD EAST MAIN CO.
100 MISSION RIDGE,
GOODLETTSVILLE, TN 37072

MADE IN INDIA